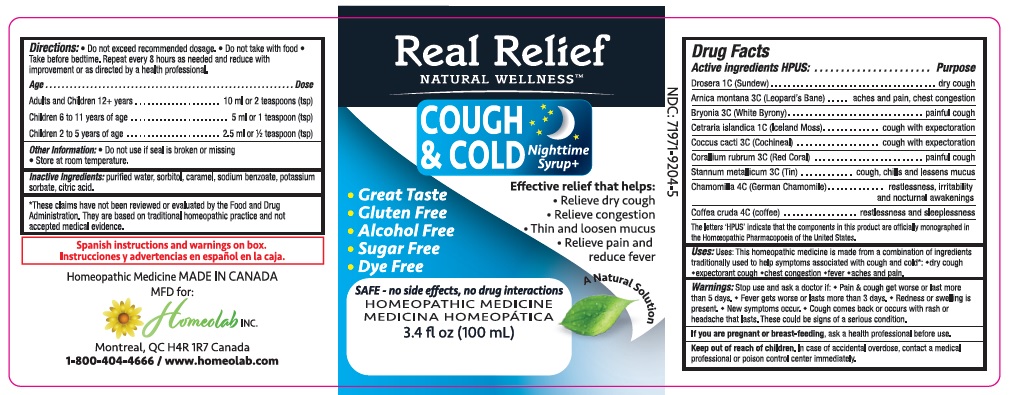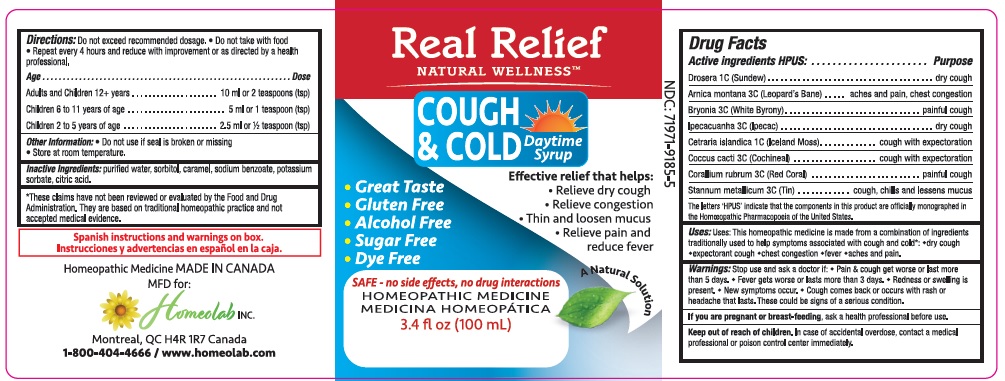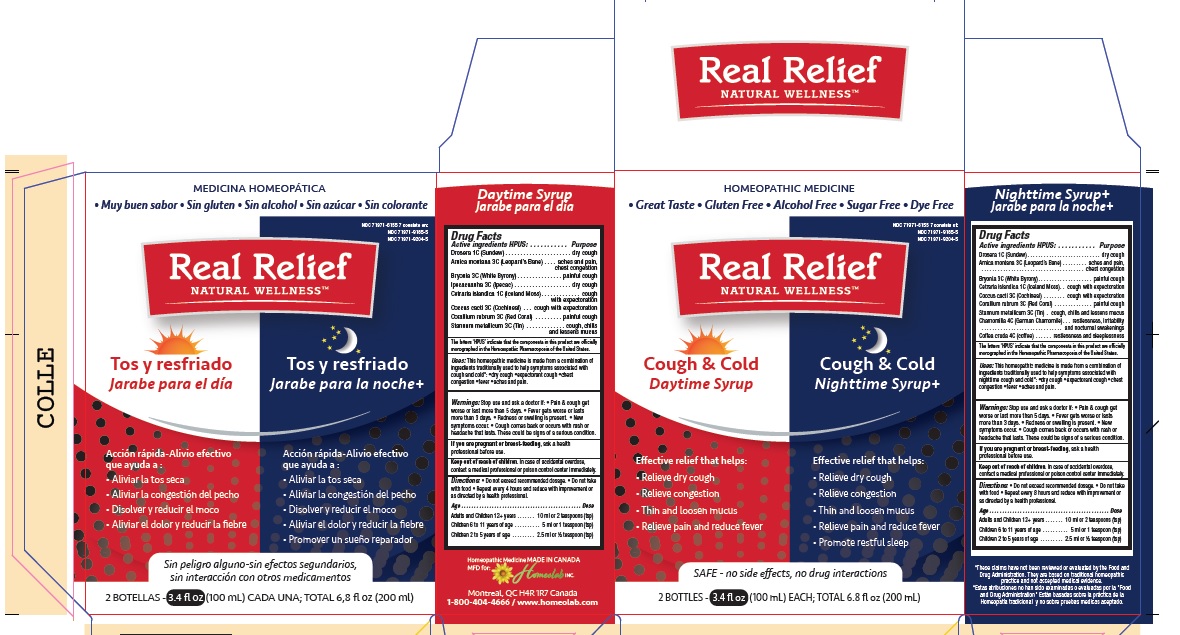 DRUG LABEL: Real Relief Natural Wellness Cough and Cold Syrup Combo Pack Daytime Formula and Nighttime Formula
NDC: 71971-6155 | Form: KIT | Route: ORAL
Manufacturer: Homeolab International (Canada) inc
Category: homeopathic | Type: HUMAN OTC DRUG LABEL
Date: 20250730

ACTIVE INGREDIENTS: DROSERA ROTUNDIFOLIA FLOWERING TOP 1 [hp_C]/100 mL; ARNICA MONTANA 3 [hp_C]/100 mL; BRYONIA ALBA WHOLE 3 [hp_C]/100 mL; IPECAC 3 [hp_C]/100 mL; CETRARIA ISLANDICA WHOLE 1 [hp_C]/100 mL; PROTORTONIA CACTI 3 [hp_C]/100 mL; CORALLIUM RUBRUM WHOLE 3 [hp_C]/100 mL; TIN 3 [hp_C]/100 mL; DROSERA ROTUNDIFOLIA FLOWERING TOP 1 [hp_C]/100 mL; ARNICA MONTANA 3 [hp_C]/100 mL; BRYONIA ALBA WHOLE 3 [hp_C]/100 mL; CETRARIA ISLANDICA WHOLE 1 [hp_C]/100 mL; PROTORTONIA CACTI 3 [hp_C]/100 mL; CORALLIUM RUBRUM WHOLE 3 [hp_C]/100 mL; TIN 3 [hp_C]/100 mL; CHAMOMILE 4 [hp_C]/100 mL; ARABICA COFFEE BEAN 4 [hp_C]/100 mL
INACTIVE INGREDIENTS: WATER; CARAMEL; SORBITOL; SODIUM BENZOATE; POTASSIUM SORBATE; CITRIC ACID MONOHYDRATE; WATER; SORBITOL; CARAMEL; SODIUM BENZOATE; POTASSIUM SORBATE; CITRIC ACID MONOHYDRATE

Active Ingredients

Part 1 -Real Relief Natural Wellness™ Cough Cold Daytime Syrup

DROSERA ROTUNDIFOLIA FLOWERING TOP
ARNICA MONTANA
BRYONIA ALBA WHOLE
IPECACUANHA (IPECAC)
CETRARIA ISLANDICA SUBSP. ISLANDICA
COCHINEAL (COCCUS CACTI)
CORALLIUM RUBRUM WHOLE
STANNUM METALLICUM (TIN)

Part 2 - Real Relief Natural Wellness™ Cough Cold Nighttime Syrup

DROSERA ROTUNDIFOLIA FLOWERING TOP
ARNICA MONTANA
BRYONIA ALBA WHOLE
CETRARIA ISLANDICA SUBSP. ISLANDICA
COCHINEAL (COCCUS CACTI)
CORALLIUM RUBRUM WHOLE
STANNUM METALLICUM (TIN)
CHAMOMILLA (GERMAN CHAMOMILLE)
COFFEA CRUDA (COFFEE)

Purpose

Part 1 - Real Relief Natural Wellness™ Cough Cold Daytime Syrup

DROSERA ROTUNDIFOLIA FLOWERING TOP Dry Cough
ARNICA MONTANA Aches and Pain , Chest Congestion
BRYONIA ALBA WHOLE Painful Cough
IPECACUANHA (IPECAC) Dry Cough
CETRARIA ISLANDICA SUBSP. ISLANDICA Cough With Expectoration
COCHINEAL (COCCUS CACTI) Cough With Expectoration
CORALLIUM RUBRUM WHOLE Painful cough
STANNUM METALLICUM (TIN) Cough, Chills and Lessen mucus

Part 2 - Real Relief Natural Wellness™ Cough Cold Nighttime Syrup

DROSERA ROTUNDIFOLIA FLOWERING TOP Dry Cough
ARNICA MONTANA Aches and Pain , Chest Congestion
BRYONIA ALBA WHOLE Painful Cough
CETRARIA ISLANDICA SUBSP. ISLANDICA Cough With Expectoration
COCHINEAL (COCCUS CACTI) Cough With Expectoration
CORALLIUM RUBRUM WHOLE Painful cough
STANNUM METALLICUM (TIN) Cough, Chills and Lessen mucus
CHAMOMILLA (GERMAN CHAMOMILLE) Restlessness, irritability and nocturnal awakening
COFFEA CRUDA (COFFEE) Restlessness and sleeplessness

The letters 'HPUS' indicate that the components in this product are officially monographed in the Homoeopathic Pharmacopoeia of the United States.

Uses

T his ho meo pathic medicine is made from a combination of ingredients traditionally used to help symptoms associated with cough and cold*; dry cough, expectorant cough, chest congestion, fever, aches and pain.

*These claims have not been reviewed by the Food and Drug Administration. They are based on traditional homeopathic practice, not medical evidence.

Warnings

Stop use and ask a doctor if: • Pain & cough get worse or last more than 5 days. • Fever gets worse or lasts more than 3 days. • Redness or swelling is present. • New symptoms occur. • cough comes back or occurs with rash or headache that lasts. These could be signs of a serious condition.

If you are pregnant or breast feeding, ask a health professional before.

Keep out of reach of children. In case of accidental overdose, contact a medical
professional or poison control center immediately.

Directions

Part 1 Real Relief Natural Wellness™ Daytime Syrup

Directions:
• Do not exceed recommended dosage
• Do not take with foods
• Repeat every 4 hours and reduce with improvement or as directed by a health professional.
Age………………………………………………………….Dose
Adults and Children 12 + years. ...........10 ml or 2 teaspoon (tsp)
Children 6 to 11 years of age. ...............5 ml or 1 teaspoon (tsp)
Children 2 to 5 years of age. .................2.5 ml or ½ teaspoon (tsp)

Part 2 Real Relief Natural Wellness™ Relief Nighttime Syrup

Directions:
• Do not exceed recommended dosage
• Do not take with foods
• Repeat every 8 hours and reduce with improvement or as directed by a health professional.
Age………………………………………………………….Dose
Adults and Children 12 + years. ............10 ml or 2 teaspoon (tsp)
Children 6 to 11 years of age. ................5 ml or 1 teaspoon (tsp)
Children 2 to 5 years of age. ..................2.5 ml or ½ teaspoon (tsp)

Other information

Part 1

Do not use if the seal is broken or missing. Store at room temperature.

Part 2

Store at room temperature.• Do not use if seal is broken or missing

*These claims have not been reviewed by the Food and Drug Administration. They are based on traditional homeopathic practice, not medical evidence.

Inactive ingredients

Purified water, sorbitol, caramel, sodium benzoate, potassium sorbate, citric acid.